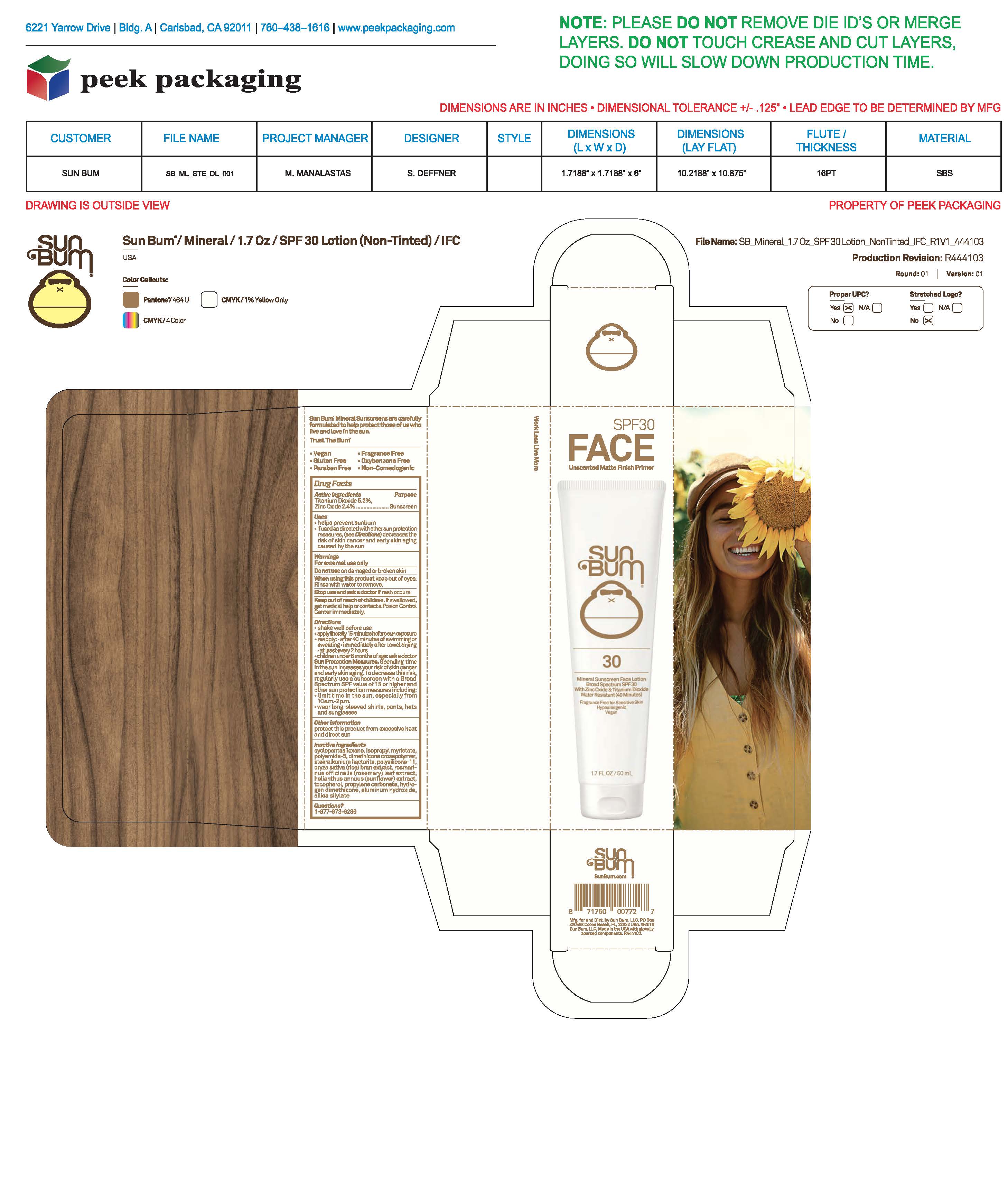 DRUG LABEL: Sun Bum 30 Mineral Sunscreen Face 1.7 OZ
NDC: 69039-759 | Form: LOTION
Manufacturer: Sun Bum, LLC
Category: otc | Type: HUMAN OTC DRUG LABEL
Date: 20250818

ACTIVE INGREDIENTS: ZINC OXIDE 24 mg/1 mL; TITANIUM DIOXIDE 53 mg/1 mL
INACTIVE INGREDIENTS: DIMETHICONE CROSSPOLYMER; ORYZA SATIVA (RICE) BRAN; ISOPROPYL MYRISTATE; ALUMINUM HYDROXIDE; HYDROGEN DIMETHICONE (13 CST); STEARALKONIUM HECTORITE; TOCOPHEROL; SILICA DIMETHYL SILYLATE; POLYAMIDE-5; ROSEMARY; HELIANTHUS ANNUUS FLOWERING TOP; CYCLOPENTASILOXANE; DIMETHICONE/VINYL DIMETHICONE CROSSPOLYMER (SOFT PARTICLE); PROPYLENE CARBONATE

Sun Bum 30 Mineral Sunscreen Face 1.7 OZ

Active ingredients

Titanium Dioxide 5.3%, Zinc Oxide 2.4%

Purpose

Sunscreen

Uses

• helps prevent sunburn • if used as directed with other sun protection measures, (see Directions) decreases the risk of skin cancer and early skin aging caused by the sun

Warnings

For external use only

Do not use on damaged or broken skin

When using this product keep out of eyes. Rinse with water to remove.

Stop use and ask a doctor if rash occurs

Keep out of reach of children. If swallowed, get medical help or contact a Poison Control Center immediately.

Warnings

Keep Out Of Reach Of Children

Directions

• shake well before use

• apply liberally 15 minutes before sun exposure

• reapply: • after 80 minutes of swimming or sweating • immediately after towel drying • at least every 2 hours

• children under 6 months of age: ask a doctor

• Sun Protection Measures. Spending time in the sun increases your risk of skin cancer and early skin aging. To decrease this risk, regularly use a sunscreen with a Broad Spectrum SPF value of 15 or higher and other sun protection measures including:

• limit time in the sun, especially from 10 a.m.- 2 p.m.

• wear long-sleeved shirts, pants, hats and sunglasses

Directions

• shake well before use

• apply liberally 15 minutes before sun exposure

Other Information

protect this product from excessive heat and direct sun

Inactive Ingredients

cyclopentasiloxane, isopropyl myristate, polyamide-5, dimethicone crosspolymer, stearalkonium hectorite, polysilicone-11, oryza sativa (rice) bran extract, rosmarinus officinalis (rosemary) leaf extract, helianthus annuus (sunflower) extract, tocopherol, propylene carbonate, hydrogen dimethicone, aluminum hydroxide, silica silylate

Questions?

1-877-978-6286